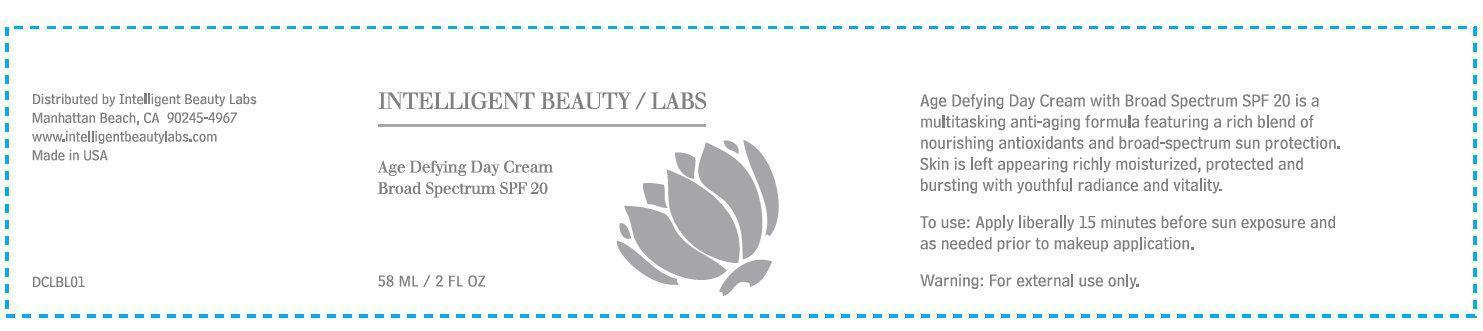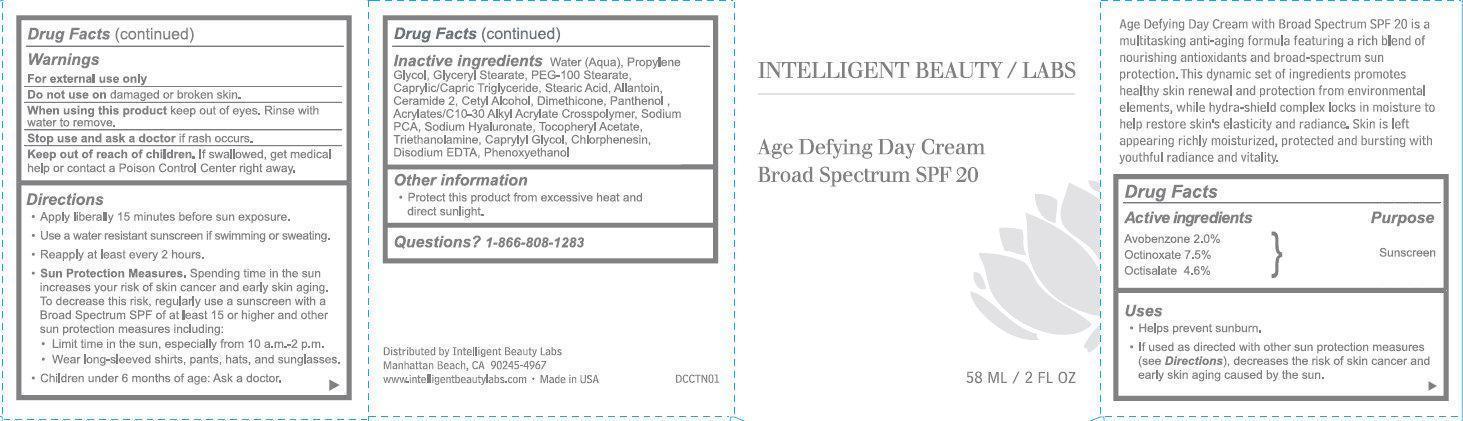 DRUG LABEL: INTELLIGENT BEAUTY LABS Age Defying Day Broad Spectrum SPF 20
NDC: 24559-001 | Form: CREAM
Manufacturer: DermStore, LLC
Category: otc | Type: HUMAN OTC DRUG LABEL
Date: 20231212

ACTIVE INGREDIENTS: AVOBENZONE 20 mg/1 mL; OCTINOXATE 75 mg/1 mL; OCTISALATE 46 mg/1 mL
INACTIVE INGREDIENTS: WATER; PROPYLENE GLYCOL; GLYCERYL MONOSTEARATE; PEG-100 STEARATE; MEDIUM-CHAIN TRIGLYCERIDES; STEARIC ACID; ALLANTOIN; CERAMIDE 2; CETYL ALCOHOL; DIMETHICONE; PANTHENOL; SODIUM PYRROLIDONE CARBOXYLATE; HYALURONATE SODIUM; .ALPHA.-TOCOPHEROL ACETATE; TROLAMINE; CAPRYLYL GLYCOL; CHLORPHENESIN; EDETATE DISODIUM; PHENOXYETHANOL

INTELLIGENT BEAUTY LABS Age Defying Day Cream Broad Spectrum SPF 20

Active ingredients

Avobenzone 2.0% Octinoxate 7.5% Octisalate 4.6%

Purpose

Sunscreen

Uses

- Helps prevent sunburn.
- If used as directed with other sun protection measures (see). Decreases the risk of skin cancer and early skin aging caused by the sun. Directions

Warnings

For external use only

Do not use on

damaged or broken skin.

When using this product

keep out of eyes. Rinse with water to remove.

Stop use and ask a doctor

if rash occurs.

Keep out of reach of children.

If swallowed, get medical help or contact a Poison Control Center right away.

Directions

- Apply liberally 15 minutes before sun exposure.
- Use a water to resistant sunscreen if swimming or sweating.
- Reapply at least every 2 hours.
- Spending time in the sun increases your risk of skin cancer and early skin aging. To decrease the risk, regularly use a sunscreen with a broad spectrum SPF of 15 or higher and other protection measures including: Sun Protection Measures.
- Limit time in the sun, especially from 10a.m - 2p.m.
- Wear long-sleeved shirts, pants, hats and sunglasses.
- Children under 6 months : Ask a doctor

Inactive ingredients

Water (Aqua), Propylene Glycol, Glyceryl stearate, PEG-100 Stearate, Caprylic/Capric Triglyceride, Stearic Acid, Allantoin, Ceramide 2, Cetyl Alcohol, Dimethicone, Panthenol, Acrylates/C10-30 Alkyl Acrylate Crosspolymer, Sodium PCA, Sodium Hyaluronate, Tocopheryl Acetate, Triethanolamine, Caprylyl Glycol, Chlorphenesin, Disodium EDTA, Phenoxyethanol.

Other information

- Protect this product from excessive heat and direct sunlight.

Questions?

1-866-808-1283

Age Defying Day Cream

with Broad Spectrum SPF 20 is a multitasking anti-aging formula featuring a rich blend of nourishing antioxidants and broad-spectrum sun protection. This dynamic set of ingredients promotes healthy skin renewal and protection from environmental elements, while hydra-shield complex locks in moisture to help restore skin's elasticity and radiance. Skin is left appearing richly moisturized, protected and bursting with youthful radiance and vitality. Distributed by Intelligent Beauty Labs Manhattan Beach, CA 90245-4967 www.intelligentbeautylabs.com - Made in USA

PACKAGE LABEL

INTELLIGENT BEAUTY / LABS Age Defying Day Cream Broad Spectrum SPF 20 58 ML / 2 FL OZ